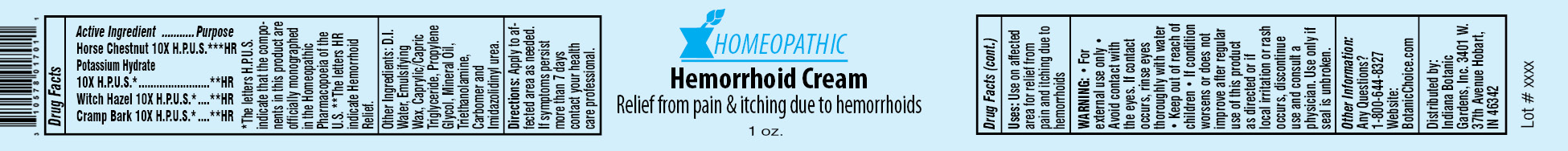 DRUG LABEL: Homeopathic Hemorrhoid
NDC: 10578-017 | Form: CREAM
Manufacturer: Indiana Botanic Gardens
Category: homeopathic | Type: HUMAN OTC DRUG LABEL
Date: 20120427

ACTIVE INGREDIENTS: HORSE CHESTNUT 10 [hp_X]/28 g; CAUSTICUM 10 [hp_X]/28 g; WITCH HAZEL 10 [hp_X]/28 g; VIBURNUM OPULUS BARK 10 [hp_X]/28 g
INACTIVE INGREDIENTS: WATER; CETOSTEARYL ALCOHOL; POLYSORBATE 60; TRICAPRYLIN; PROPYLENE GLYCOL; MINERAL OIL; TROLAMINE; CARBOMER 934; IMIDUREA

Homeopathic Hemorrhoid Cream

Active Ingredients

Horse Chestnut 10X H.P.U.S.*

Potassium Hydrate 10X H.P.U.S.*

Witch Hazel 10X H.P.U.S.*

Cramp Bark 10X H.P.U.S.*

Purpose

**HR

**HR

**HR

**HR

*The letters H.P.U.S. indicate that the components in this product are officially monographed in the Homeopathic Pharmacopoeia of the U.S. **The letters HR indicate Hemorrhoid Relief.

Other Ingredients:

D.I. Water, Emulsifying Wax, Caprylic/Capric Triglyceride, Propylene Glycol, Mineral Oil, Triethanolamine, Carbomer and Imidazolidinyl urea.

Directions:

Apply to affected area as needed. If symptoms persist more than 7 days contact your health care professional.

Uses:

Use on affected area for relief from pain and itching due to hemorrhoids

WARNING:

- for external use only
- Avoid contact with the eyes. If contact occurs, rinse eyes thoroughly with water

- Keep out of reach of children

STOP USE

- If condition worsens or does not improve after regular use of this product as directed or if local irritation or rash occurs, discontinue use and consult a physician.

Use only if seal is unbroken.

Other Information:

Any Questions?

1-800-644-8327

Website:

BotanicChoice.com

Distributed by:

Indiana Botanic Gardens, Inc. 3401 W. 37th Avenue Hobart, IN 46342

Homeopathic Hemorrhoid Cream

Relief from pain & itching due to hemorrhoids

1 oz.